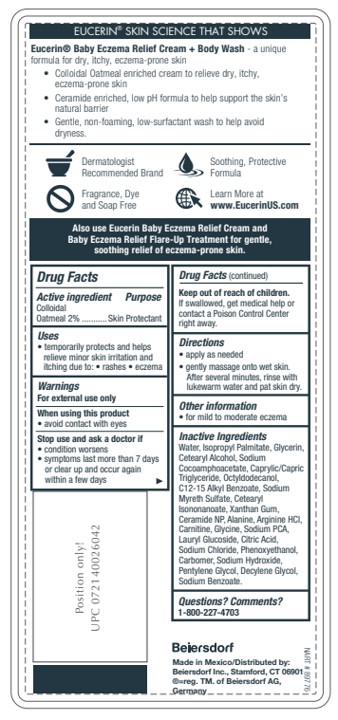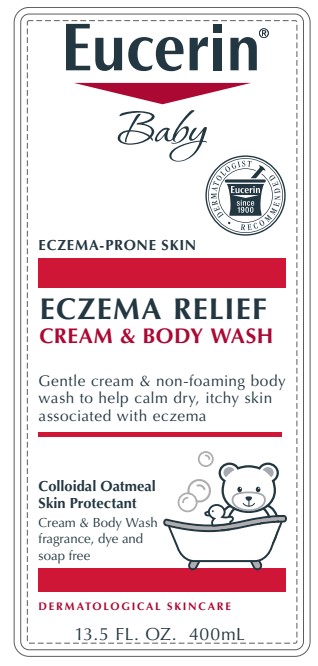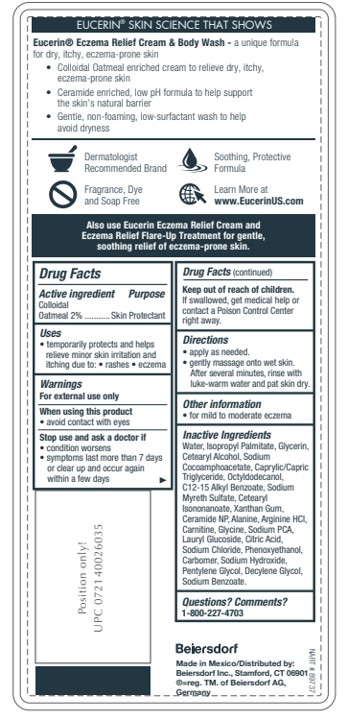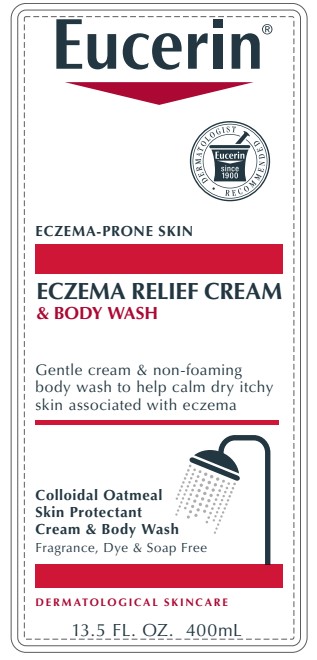 DRUG LABEL: Eczema Relief Cream Body Wash
NDC: 10356-382 | Form: LOTION
Manufacturer: Beiersdorf Inc
Category: otc | Type: HUMAN OTC DRUG LABEL
Date: 20251231

ACTIVE INGREDIENTS: OATMEAL 2 g/100 mL
INACTIVE INGREDIENTS: SODIUM COCOAMPHOACETATE; SODIUM CHLORIDE; DECYLENE GLYCOL; SODIUM HYDROXIDE; LAURYL GLUCOSIDE; PENTYLENE GLYCOL; CETOSTEARYL ALCOHOL; ALKYL (C12-15) BENZOATE; CETEARYL ISONONANOATE; XANTHAN GUM; GLYCINE; CARBOMER 980; SODIUM MYRETH SULFATE; SODIUM PYRROLIDONE CARBOXYLATE; ISOPROPYL PALMITATE; ARGININE HYDROCHLORIDE; CARNITINE; SODIUM BENZOATE; OCTYLDODECANOL; WATER; GLYCERIN; MEDIUM-CHAIN TRIGLYCERIDES; CERAMIDE 3; PHENOXYETHANOL; CITRIC ACID MONOHYDRATE; ALANINE

Eucerin Eczema Relief Cream & Body Wash

Active ingredients
Colloidal Oatmeal 2%

Warnings
For external use only

When using this product avoid contact with eyes

Stop use and ask a doctor if
condition worsens
symptoms last more than 7 days or clear up and occur again within a few days

Keep out of reach of children. If swallowed, get medical help or
contact a Poison Control Center right away.

Uses
temporarily protects and helps relieve minor skin irritation and itching
due to rashes, eczema

Directions
apply as needed

gently massage onto wet skin. After several minutes, rinse with lukewarm water and pat skin dry.

Questions or comments?
1-800-227-4703

Inactive Ingredients
Water, Isopropyl Palmitate, Glycerin,
Cetearyl Alcohol, Sodium
Cocoamphoacetate, Caprylic/Capric
Triglyceride, Octyldodecanol,
C12-15 Alkyl Benzoate, Sodium
Myreth Sulfate, Cetearyl
Isononanoate, Xanthan Gum,
Ceramide NP, Alanine, Arginine HCl,
Carnitine, Glycine, Sodium PCA,
Lauryl Glucoside, Citric Acid,
Sodium Chloride, Phenoxyethanol,
Carbomer, Sodium Hydroxide,
Pentylene Glycol, Decylene Glycol,
Sodium Benzoate.

PURPOSE

Skin protectant

PACKAGE LABEL

Eucerin

Eczema Relief Cream & Body Wash

Eczema Prone Skin

Gentle cream and non-foaming body wash
to help calm dry, itchy skin
associated with eczema

Colloidal Oatmeal Skin Protectant Cream

and Body Wash

Fragrance, Dye & Soap Free

Dermatological Skincare

Eucerin Dermatologist Recommended

Eucerin Baby

Eczema Relief Cream & Body Wash

Eczema Prone Skin

Gentle cream and non-foaming body wash
to help calm dry, itchy skin
associated with eczema

Colloidal Oatmeal Skin Protectant Cream

and Body Wash

Fragrance, Dye & Soap Free

Dermatological Skincare

Eucerin Dermatologist Recommended